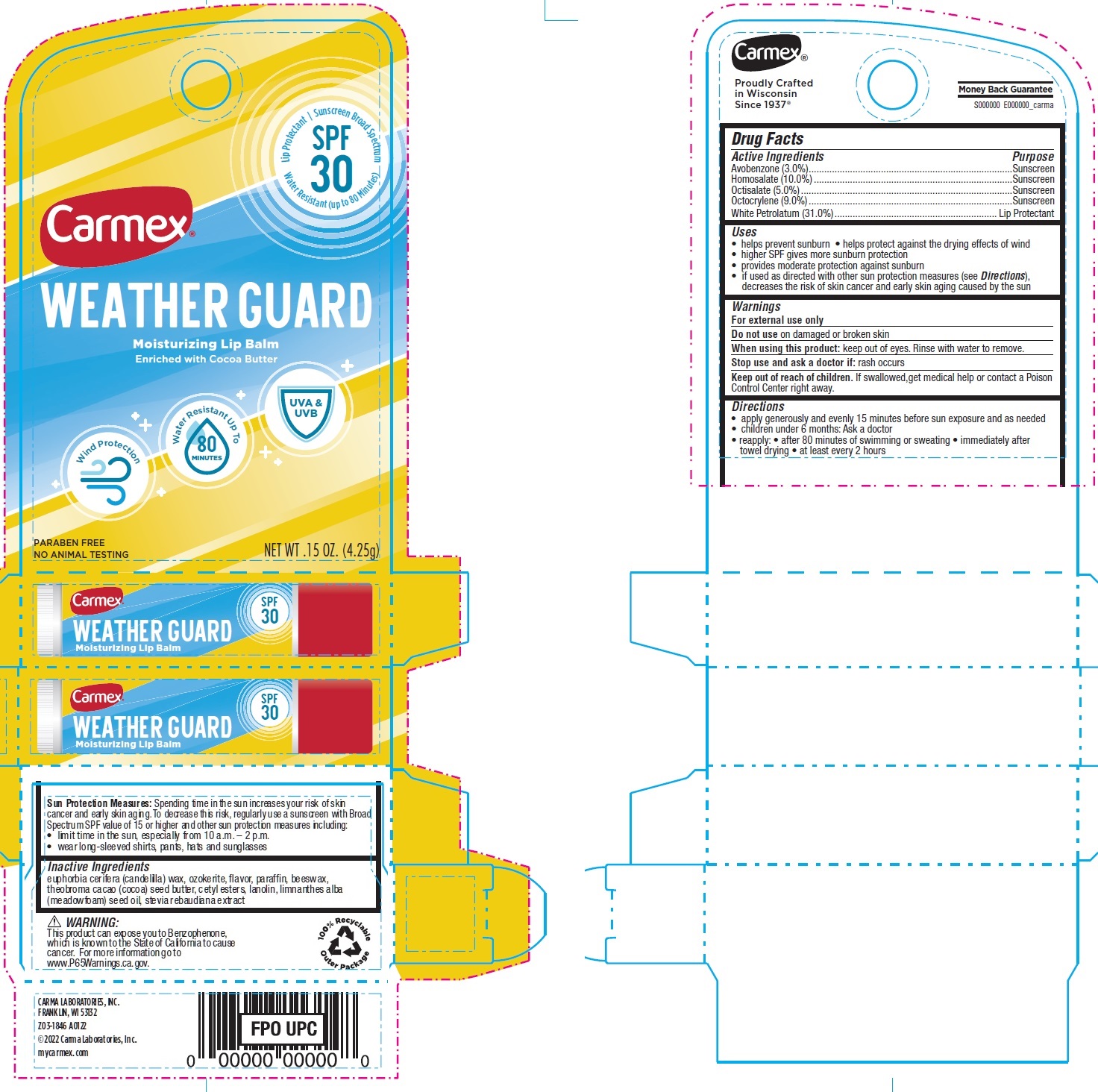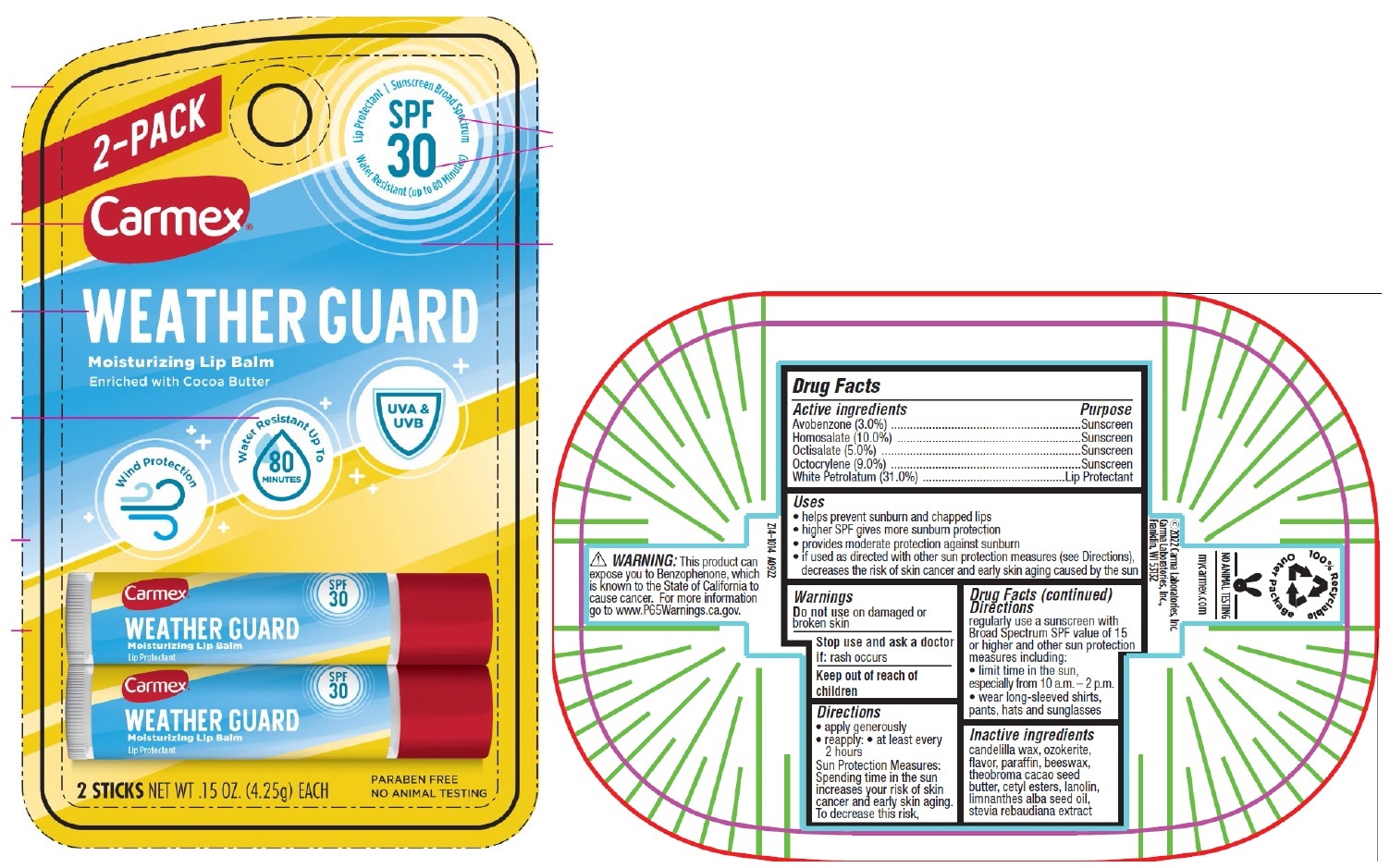 DRUG LABEL: Carmex Weather Guard Moisturizing Lip Balm SPF 30
NDC: 10210-0056 | Form: SALVE
Manufacturer: Carma Laboratories, Inc.
Category: otc | Type: HUMAN OTC DRUG LABEL
Date: 20231025

ACTIVE INGREDIENTS: AVOBENZONE 30 mg/1 g; HOMOSALATE 100 mg/1 g; OCTISALATE 50 mg/1 g; OCTOCRYLENE 90 mg/1 g; WHITE PETROLATUM 310 mg/1 g
INACTIVE INGREDIENTS: CANDELILLA WAX; PARAFFIN; YELLOW WAX; COCOA BUTTER; CETYL ESTERS WAX; LANOLIN; MEADOWFOAM SEED OIL

Carmex Weather Guard Moisturizing Lip Balm SPF 30

Active Ingredients

Avobenzone (3.0%)

Homosalate (10.0%)

Octisalate (5.0%)

Octocrylene (9.0%)

White Petrolatum (31.0%)

Purpose

Sunscreen

Lip Protectant

Uses

• helps prevent sunburn • helps protect against the drying effects of wind • higher SPF gives more sunburn protection • provides moderate protection against sunburn • if used as directed with other sun protection measures (see Directions), decreases the risk of skin cancer and early skin aging caused by the sun

Warnings

For external use only

Do not use

on damaged or broken skin

When using this product:

keep out of eyes. Rinse with water to remove.

Stop use and ask a doctor if:

rash occurs

Keep out of reach of children.

If swallowed,get medical help or contact a Poison Control Center right away.

Directions

• apply generously and evenly 15 minutes before sun exposure and as needed • children under 6 months: Ask a doctor • reapply: • after 80 minutes of swimming or sweating • immediately after towel drying • at least every 2 hours

Spending time in the sun increases your risk of skin cancer and early skin aging. To decrease this risk, regularly use a sunscreen with Broad Spectrum SPF value of 15 or higher and other sun protection measures including: • limit time in the sun, especially from 10 a.m. – 2 p.m. • wear long-sleeved shirts, pants, hats and sunglasses Sun Protection Measures:

Inactive Ingredients

euphorbia cerifera (candelilla) wax, ozokerite, flavor, paraffin, beeswax, theobroma cacao (cocoa) seed butter, cetyl esters, lanolin, limnanthes alba (meadowfoam) seed oil, stevia rebaudiana extract